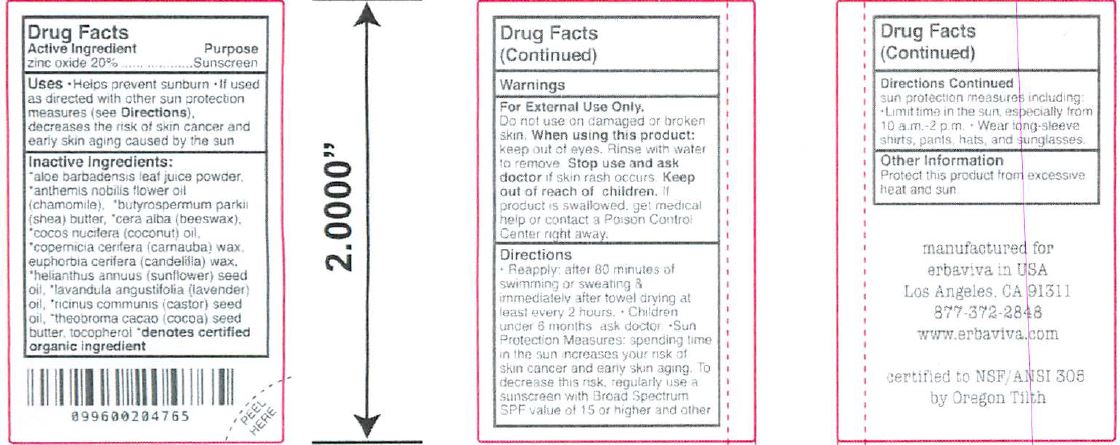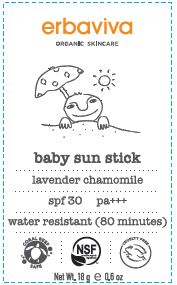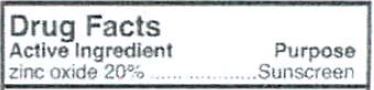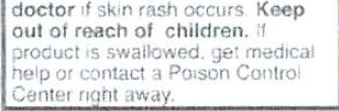 DRUG LABEL: Sunscreen
NDC: 62932-230 | Form: STICK
Manufacturer: Private Label Select Ltd CO
Category: otc | Type: HUMAN OTC DRUG LABEL
Date: 20201229

ACTIVE INGREDIENTS: ZINC OXIDE 20 g/100 g
INACTIVE INGREDIENTS: CANDELILLA WAX; CARNAUBA WAX; WHITE WAX; COCONUT OIL; SUNFLOWER OIL; SHEA BUTTER; ALOE VERA LEAF; .GAMMA.-TOCOPHEROL; CHAMAEMELUM NOBILE FLOWER OIL; CASTOR OIL; LAVENDER OIL; COCOA BUTTER; .DELTA.-TOCOPHEROL; .ALPHA.-TOCOPHEROL, D-; .BETA.-TOCOPHEROL

Erbaviva Baby Sun Stick SPF 30, Lavender & Chamomile